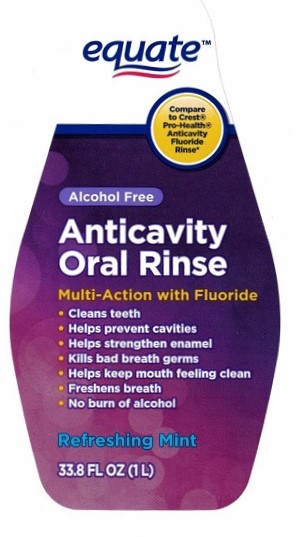 DRUG LABEL: Equate Anticavity Oral Rinse
NDC: 49035-535 | Form: LIQUID
Manufacturer: Wal-Mart Stores, Inc.
Category: otc | Type: HUMAN OTC DRUG LABEL
Date: 20230106

ACTIVE INGREDIENTS: SODIUM FLUORIDE 0.021 g/1 mL
INACTIVE INGREDIENTS: D&C RED NO. 33; FD&C RED NO. 3; WATER; GLYCERIN; CETYLPYRIDINIUM CHLORIDE; POLOXAMER 407; PHOSPHORIC ACID; METHYLPARABEN; SACCHARIN SODIUM; PROPYLPARABEN; PROPYLENE GLYCOL; SODIUM PHOSPHATE, DIBASIC

Equate Anticavity Oral Rinse

Drug Facts

Active ingredient

Sodium fluoride 0.021%

(0.01% w/v fluoride ion)

Purpose

Anticavity

INDICATIONS AND USAGE

Use aids in the prevention of dental cavities

Warnings

Keep out of reach of children under 6 years of age. If more than used for rinsing is accidentally swallowed, get medical help or contact a Poison Control Center right away.

Directions

- Adults and children 6 years and older: use twice a day after brushing your teeth with a toothpaste
- vigorously swish 10 mL (2 teaspoonfuls) of rinse between your teeth for 1 minute and then spit out.
- do not swallow the rinse
- do not eat or drink for 30 minutes after rinsing
- instruct children under 12 years of age in good rinsing habits (to minimize swallowing)
- supervise childrenas necessary until capable of using without supervision
- children under 6 years of age: consult a dentist or doctor

INACTIVE INGREDIENT

Inactive ingredients water, glycerin, flavor, cetylpyridinium chloride, poloxamer 407, phosphoric acid, methylparaben, sodium saccharin, propylparaben, propylene glycol, disodium phosphate, red 33, green3

Questions? Call 1-888-287-1915

DISTRIBUTED BY: Wal-Mart Stores, Inc., Bentonville, AR 72716

PRODUCT OF CANADA

PACKAGE LABEL

equate™

Anticavity Oral Rinse

Multi-Action with Fluoride

33.8 FL OZ (1L)